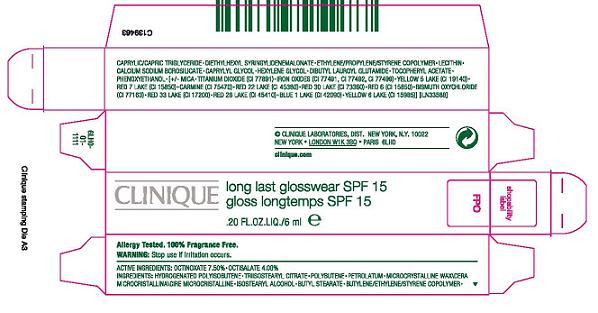 DRUG LABEL: LONG LAST GLOSSWEAR
NDC: 49527-743 | Form: LIQUID
Manufacturer: CLINIQUE LABORATORIES INC
Category: otc | Type: HUMAN OTC DRUG LABEL
Date: 20100405

ACTIVE INGREDIENTS: OCTINOXATE 7.5 mL/100 mL; OCTISALATE 4.0 mL/100 mL

active ingredients: octinoxate 7.50% [] octisalate 4.00%

WARNINGS

warning: stop use if irritation occurs

PACKAGE LABEL

PRINCIPAL DISPLAY PANEL:

CLINIQUE
LONG LAST GLOSSWEAR SPF 15
0.20 FL OZ LIQ/6 ML
CLINIQUE LABORATORIES DIST.
NEW YORK, NY 10022
WWW.CLINIQUE.COM
6LH0